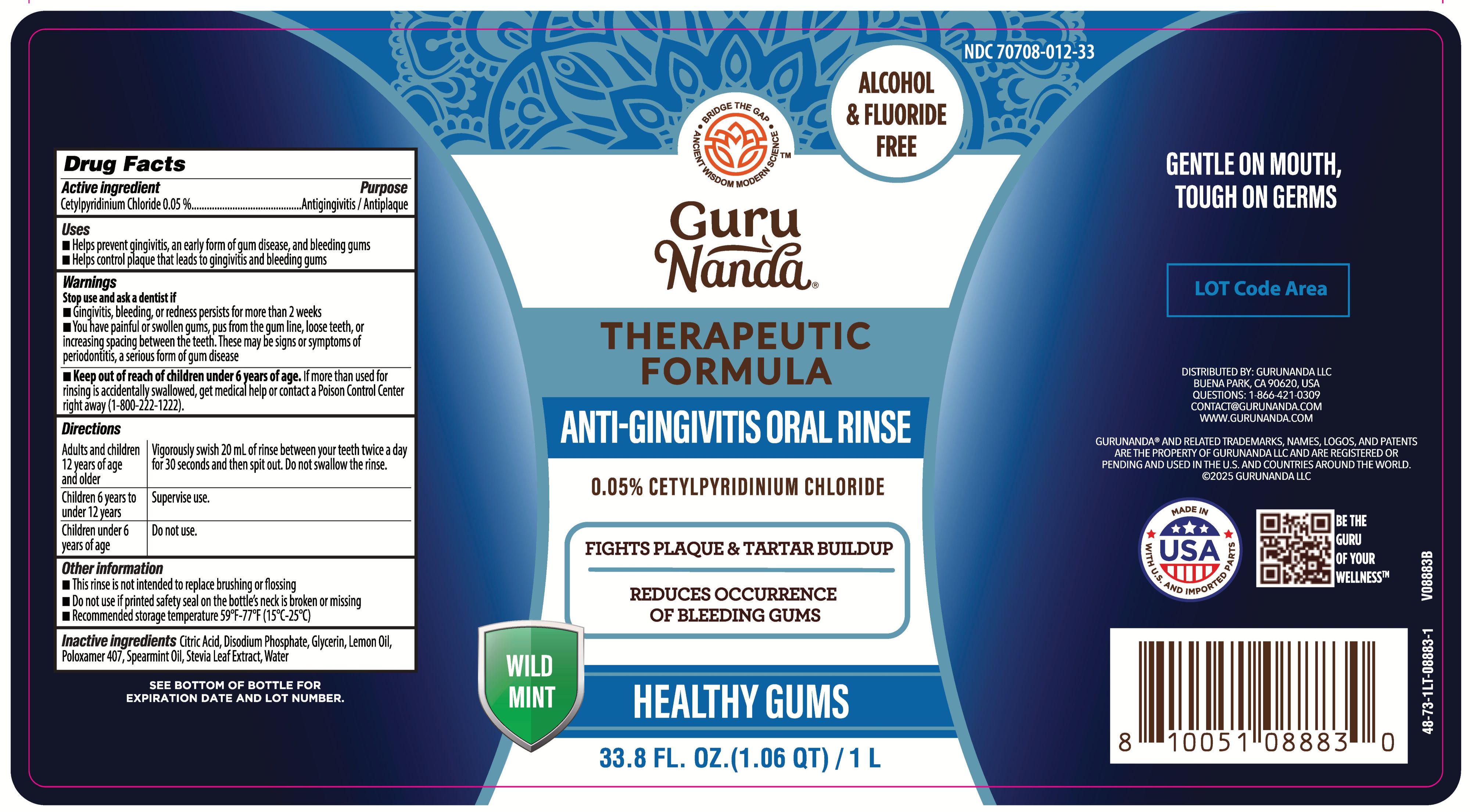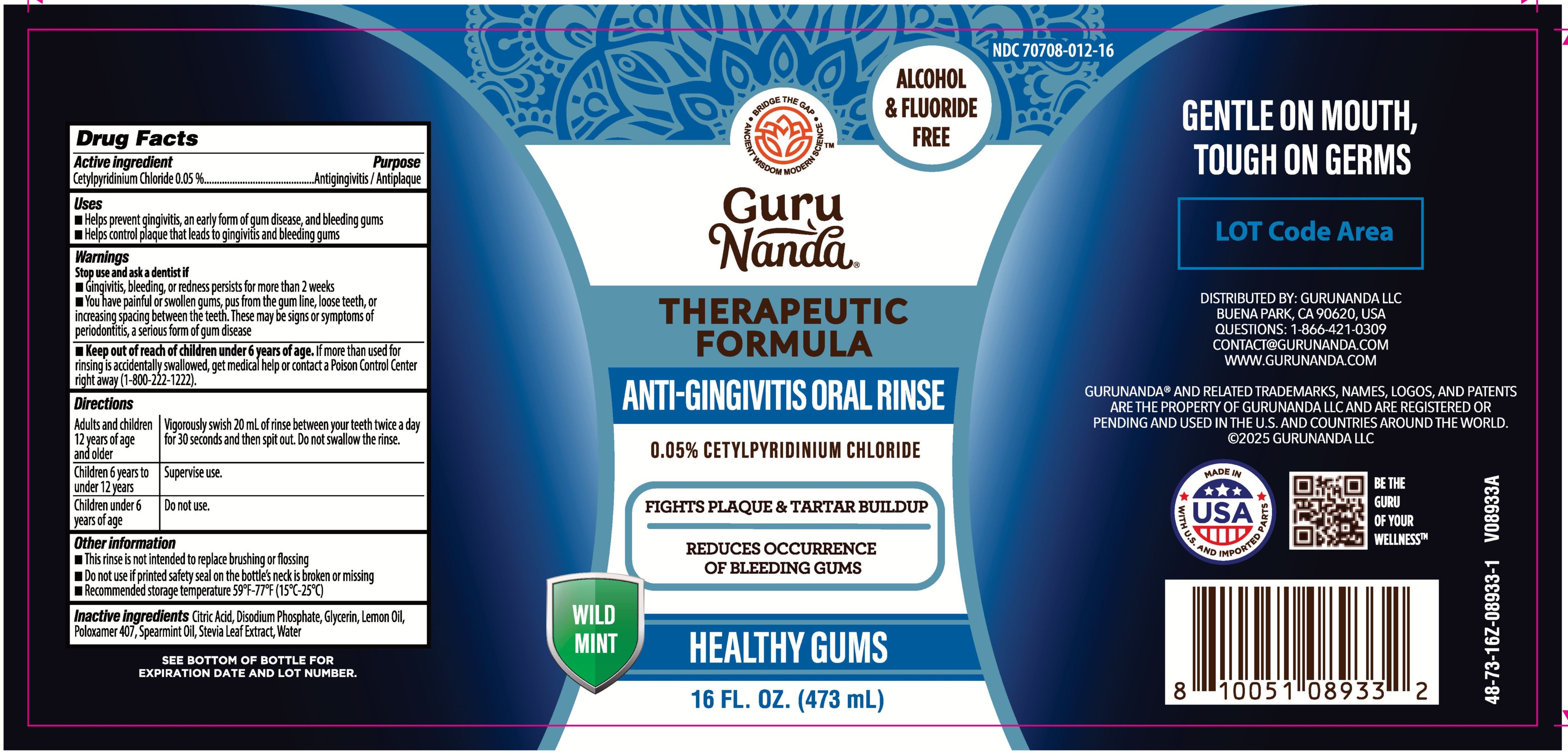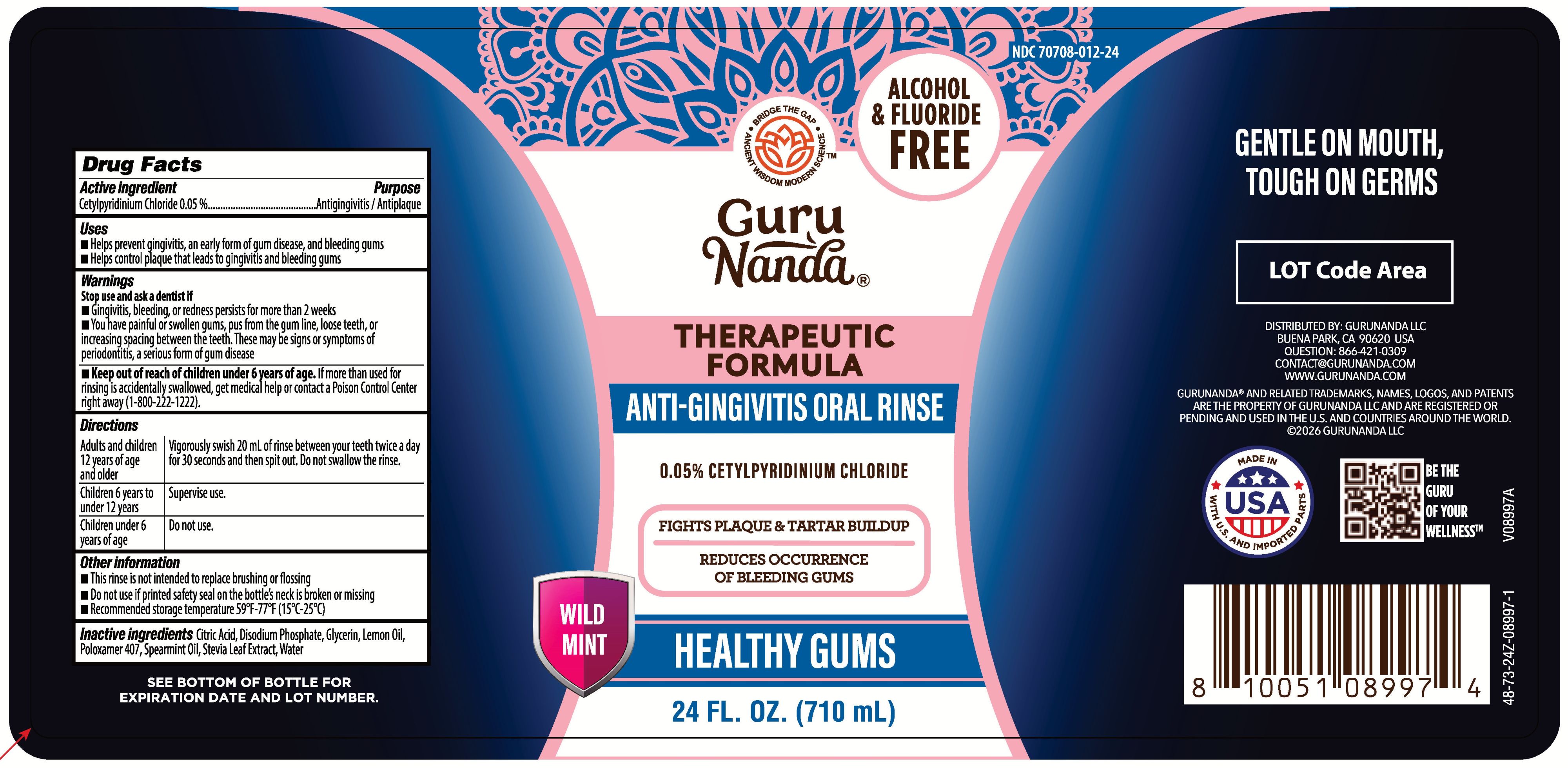 DRUG LABEL: GuruNanda Anti-Gingivitis
NDC: 70708-012 | Form: RINSE
Manufacturer: GURUNANDA, LLC
Category: otc | Type: HUMAN OTC DRUG LABEL
Date: 20260119

ACTIVE INGREDIENTS: CETYLPYRIDINIUM CHLORIDE 0.05 g/1 mL
INACTIVE INGREDIENTS: DISODIUM PHOSPHATE; GLYCERIN; STEVIA LEAF; CITRIC ACID; POLOXAMER 407; WATER; SPEARMINT OIL; LEMON OIL

GN Anti-Gingivitis Oral Rinse

Active Ingredient

Cetylpyridinium Chloride 0.05%

Purpose

Antigingivitis/Antiplaque

Uses

- Helps prevent gingivitis, an early form of gum disease, and bleeding gums
- Helps control plaque that leads to gingivitis and bleeding gums

Warnings

Stop use and ask a dentist if

- Gingivitis, bleeding, or redness persists for more than 2 weeks
- You have painful or swollen gums, pus from the gum line, loose teeth, or increasing spacing between the teeth. These may be signs or symptoms of periodontits, a serious form of gum disease

Keep out of reach of children under 6 years of age.

If more than used for rinsing is accidentally swallowed, get medical help or contact a Poison Control Center right away (1-800-222-1222).

Directions

Adults and children 12 years of age and older: Vigorously swish 20 mL (4 teaspoonfuls) of rinse between your teeth twice a day for 30 seconds and then spit out. Do not swallow the rinse.

Children 6 years to under 12 years: Supervise use.

Children under 6 years of age: Do not use.

Other Information

- Do not use if printed safety seal on the bottle's neck is broken or missing
- Recommended storage temperature 59°F-77°F (15°C-25°C)

Inactive Ingredients

Citric Acid, Disodium Phosphate, Glycerin, Lemon Oil, Poloxamer 407, Spearmint Oil, Stevia Leaf Extract, Water